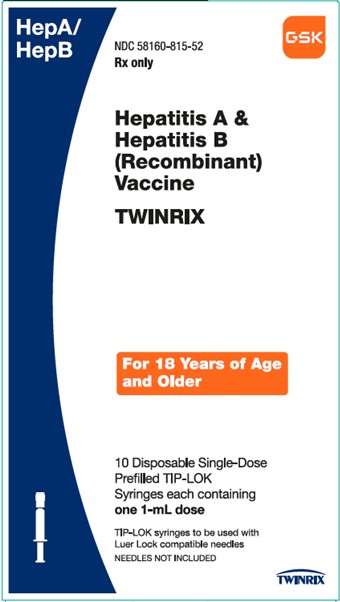 DRUG LABEL: TWINRIX
NDC: 58160-815 | Form: INJECTION, SUSPENSION
Manufacturer: GlaxoSmithKline Biologicals SA
Category: other | Type: VACCINE LABEL
Date: 20240531

ACTIVE INGREDIENTS: HEPATITIS A VIRUS STRAIN HM175 ANTIGEN (FORMALDEHYDE INACTIVATED) 720 [iU]/1 mL; HEPATITIS B VIRUS SUBTYPE ADW2 HBSAG SURFACE PROTEIN ANTIGEN 20 ug/1 mL
INACTIVE INGREDIENTS: ALUMINUM PHOSPHATE; ALUMINUM HYDROXIDE; SODIUM CHLORIDE; POLYSORBATE 20; WATER; FORMALDEHYDE; NEOMYCIN SULFATE

HIGHLIGHTS OF PRESCRIBING INFORMATION

These highlights do not include all the information needed to use TWINRIX safely and effectively. See full prescribing information for TWINRIX.
TWINRIX [Hepatitis A & Hepatitis B (Recombinant) Vaccine] injectable suspension, for intramuscular use
Initial U.S. Approval: 2001

1 INDICATIONS AND USAGE

TWINRIX is a vaccine indicated for active immunization against disease caused by hepatitis A virus and infection by all known subtypes of hepatitis B virus. TWINRIX is approved for use in persons 18 years of age or older. (1)

2 DOSAGE AND ADMINISTRATION

- TWINRIX is administered by intramuscular injection. (2.2)
- Standard Dosing: A series of 3 doses (1 mL each) given on a 0-, 1-, and 6-month schedule. (2.3)
- Accelerated Dosing: A series of 4 doses (1-mL each) given on Days 0, 7, and 21 to 30 followed by a booster dose at Month 12. (2.3)

3 DOSAGE FORMS AND STRENGTHS

Suspension for injection available in 1-mL prefilled syringes. (3, 11, 16)

4 CONTRAINDICATIONS

Severe allergic reaction (e.g., anaphylaxis) after a previous dose of any hepatitis A-containing or hepatitis B-containing vaccine, or to any component of TWINRIX, including yeast and neomycin. (4)

5 WARNINGS AND PRECAUTIONS

Syncope (fainting) can occur in association with administration of injectable vaccines, including TWINRIX. Procedures should be in place to avoid falling injury and to restore cerebral perfusion following syncope. (5.1)

6 ADVERSE REACTIONS

Following any dose of TWINRIX, the most common (≥10%) solicited injection site reactions were injection site soreness (35% to 41%) and redness (8% to 11%); the most common solicited systemic adverse reactions were headache (13% to 22%) and fatigue (11% to 14%). (6.1)

To report SUSPECTED ADVERSE REACTIONS, contact GlaxoSmithKline at 1-888-825-5249 or VAERS at 1-800-822-7967 or www.vaers.hhs.gov.

7 DRUG INTERACTIONS

Do not mix TWINRIX with any other vaccine or product in the same syringe. (7.1)

FULL PRESCRIBING INFORMATION

1 INDICATIONS AND USAGE

TWINRIX is indicated for active immunization against disease caused by hepatitis A virus and infection by all known subtypes of hepatitis B virus. TWINRIX is approved for use in persons 18 years of age or older.

2 DOSAGE AND ADMINISTRATION

2.1 Preparation for Administration

The vaccine should be re-suspended before use. When re-suspended, the vaccine will have a uniform hazy white appearance.

Upon storage, a fine white deposit with a clear colorless layer above may be present. Re-suspend the vaccine following the steps below.

1. Hold the syringe upright in a closed hand.
2. Shake the syringe by tipping it upside down and back upright again.
3. Repeat this action vigorously for at least 15 seconds.
4. Inspect the vaccine again:
  1. If the vaccine appears as a uniform hazy white suspension, it is ready to use – the appearance should not be clear.
  2. If the vaccine still does not appear as a uniform hazy white suspension, tip upside down and back upright again for at least another 15 seconds then inspect again.

Parenteral drug products should be inspected visually for particulate matter and discoloration prior to administration, whenever solution and container permit. If either of these conditions exists, the vaccine should not be administered.

Attach a sterile needle to the prefilled syringe and administer intramuscularly.

2.2 Administration

TWINRIX should be administered by intramuscular injection only as a 1-mL dose. Administer in the deltoid region. Do not administer in the gluteal region; such injections may result in a suboptimal response.

Do not administer this product intravenously, intradermally, or subcutaneously.

2.3 Recommended Dose and Schedule

Standard dosing schedule consists of 3 doses (1-mL each), given intramuscularly at 0, 1, and 6 months. Alternatively, an accelerated schedule of 4 doses (1-mL each), given intramuscularly on Days 0, 7, and 21 to 30 followed by a booster dose at Month 12 may be used.

3 DOSAGE FORMS AND STRENGTHS

Suspension for injection available in 1-mL prefilled TIP-LOK syringes [see Description (11), How Supplied/Storage and Handling (16)].

4 CONTRAINDICATIONS

Severe allergic reaction (e.g., anaphylaxis) after a previous dose of any hepatitis A-containing or hepatitis B-containing vaccine, or to any component of TWINRIX, including yeast and neomycin, is a contraindication to administration of TWINRIX [see Description (11)].

5 WARNINGS AND PRECAUTIONS

5.1 Syncope

Syncope (fainting) can occur in association with administration of injectable vaccines, including TWINRIX. Syncope can be accompanied by transient neurological signs such as visual disturbance, paresthesia, and tonic-clonic limb movements. Procedures should be in place to avoid falling injury and to restore cerebral perfusion following syncope.

5.2 Preventing and Managing Allergic Vaccine Reactions

Prior to immunization, the healthcare provider should review the immunization history for possible vaccine sensitivity and previous vaccination-related adverse reactions to allow an assessment of benefits and risks. Appropriate medical treatment and supervision must be available to manage possible anaphylactic reactions following administration of the vaccine. [See Contraindications (4).]

5.3 Moderate or Severe Acute Illness

To avoid diagnostic confusion between manifestations of an acute illness and possible vaccine adverse effects, vaccination with TWINRIX should be postponed in persons with moderate or severe acute febrile illness unless they are at immediate risk of hepatitis A or hepatitis B infection.

5.4 Altered Immunocompetence

Immunocompromised persons, including individuals receiving immunosuppressive therapy, may have a diminished immune response to TWINRIX.

5.5 Multiple Sclerosis

Results from 2 clinical studies indicate that there is no association between hepatitis B vaccination and the development of multiple sclerosis,^1 and that vaccination with hepatitis B vaccine does not appear to increase the short-term risk of relapse in multiple sclerosis.^2

5.6 Limitations of Vaccine Effectiveness

Hepatitis A and hepatitis B have relatively long incubation periods. The vaccine may not prevent hepatitis A or hepatitis B infection in individuals who have an unrecognized hepatitis A or hepatitis B infection at the time of vaccination. Additionally, vaccination with TWINRIX may not protect all individuals.

6 ADVERSE REACTIONS

6.1 Clinical Trials Experience

Because clinical trials are conducted under widely varying conditions, adverse reaction rates observed in the clinical trials of a vaccine cannot be directly compared with rates in the clinical trials of another vaccine and may not reflect the rates observed in practice.

Following any dose of TWINRIX, the most common (≥10%) solicited injection site reactions were injection site soreness (35% to 41%) and redness (8% to 11%); the most common solicited systemic adverse reactions were headache (13% to 22%) and fatigue (11% to 14%).

The safety of TWINRIX has been evaluated in clinical trials involving the administration of approximately 7,500 doses to more than 2,500 individuals.

In a U.S. study, 773 subjects (aged 18 to 70 years) were randomized 1:1 to receive TWINRIX
(0-, 1-, and 6-month schedule) or concurrent administration of ENGERIX-B (0-, 1-, and 6-month schedule) and HAVRIX (0- and 6-month schedule). Solicited local adverse reactions and systemic adverse events were recorded by parents/guardians on diary cards for 4 days (Days 0 to 3) after vaccination. Unsolicited adverse events were recorded for 31 days after vaccination. Solicited reactions reported following the administration of TWINRIX or ENGERIX-B and HAVRIX are presented in Table 1.

Table 1. Rates of Local Adverse Reactions and Systemic Adverse Reactions within 4 Days of Vaccinationa with TWINRIXb or ENGERIX-B and HAVRIXc
Local | TWINRIX |  |  | ENGERIX-B |  |  | HAVRIX
Local | Dose 1 | Dose 2 | Dose 3 | Dose 1 | Dose 2 | Dose 3 | Dose 1 | Dose 2
Local | (n = 385); % | (n = 382); % | (n = 374); % | (n = 382); % | (n = 376); % | (n = 369); % | (n = 382); % | (n = 369); %
Soreness | 37 | 35 | 41 | 41 | 25 | 30 | 53 | 47
Redness | 8 | 9 | 11 | 6 | 7 | 9 | 7 | 9
Swelling | 4 | 4 | 6 | 3 | 5 | 5 | 5 | 5
Systemic | TWINRIX |  |  | ENGERIX-B and HAVRIX
Systemic | Dose 1 | Dose 2 | Dose 3 | Dose 1d |  | Dose 2e |  | Dose 3d
Systemic | (n = 385); % | (n = 382); % | (n = 374); % | (n = 382); % |  | (n = 376); % |  | (n = 369); %
Headache | 22 | 15 | 13 | 19 |  | 12 |  | 14
Fatigue | 14 | 13 | 11 | 14 |  | 9 |  | 10
Diarrhea | 5 | 4 | 6 | 5 |  | 3 |  | 3
Nausea | 4 | 3 | 2 | 7 |  | 3 |  | 5
Fever | 4 | 3 | 2 | 4 |  | 2 |  | 4
Vomiting | 1 | 1 | 0 | 1 |  | 1 |  | 1
a Within 4 days of vaccination defined as day of vaccination and the next 3 days.
b 389 subjects received at least 1 dose of TWINRIX.
c 384 subjects received at least 1 dose each of ENGERIX-B and HAVRIX.
d Doses 1 and 3 included ENGERIX-B and HAVRIX in the control group receiving separate vaccinations.
e Dose 2 included only ENGERIX-B in the control group receiving separate vaccinations.

Most solicited local adverse reactions and systemic adverse reactions seen with TWINRIX were considered by the subjects as mild and self-limiting and did not last more than 48 hours.

In a clinical trial in which TWINRIX was given on a 0-, 7-, and 21- to 30-day schedule followed by a booster dose at 12 months, solicited local adverse reactions or systemic adverse reactions were comparable to those seen in other clinical trials of TWINRIX given on a 0-, 1-, and 6-month schedule.

Among 2,299 subjects in 14 clinical trials, the following adverse reactions were reported to occur within 30 days following vaccination:

Incidence 1% to 10% of Injections, Seen in Clinical Trials with TWINRIX

Infections and Infestations: Upper respiratory tract infections.

General Disorders and Administration Site Conditions: Injection site induration.

Incidence <1% of Injections, Seen in Clinical Trials with TWINRIX

Infections and Infestations: Respiratory tract illnesses.

Metabolism and Nutrition Disorders: Anorexia.

Psychiatric Disorders: Agitation, insomnia.

Nervous System Disorders: Dizziness, migraine, paresthesia, somnolence, syncope.

Ear and Labyrinth Disorders: Vertigo.

Vascular Disorders: Flushing.

Gastrointestinal Disorders: Abdominal pain, vomiting.

Skin and Subcutaneous Tissue Disorders: Erythema, petechiae, rash, sweating, urticaria.

Musculoskeletal and Connective Tissue Disorders: Arthralgia, back pain, myalgia.

General Disorders and Administration Site Conditions: Injection site ecchymosis, injection site pruritus, influenza-like symptoms, irritability, weakness.

Incidence <1% of Injections, Seen in Clinical Trials with HAVRIX and/or ENGERIX-B

Blood and Lymphatic System Disorders: Lymphadenopathy.a+b

Nervous System Disorders: Dysgeusia,a hypertonia,a tingling.b

Eye Disorders: Photophobia.a

Vascular Disorders: Hypotension.b

Gastrointestinal Disorders: Constipation.b

Investigations: Creatine phosphokinase increased.a

a+b Following either HAVRIX or ENGERIX-B.

a Following HAVRIX.

b Following ENGERIX-B.

Adverse reactions within 30 days of vaccination in the U.S. clinical trial of TWINRIX given on a 0-, 7-, and 21- to 30-day schedule followed by a booster dose at 12 months were comparable to those reported in other clinical trials.

6.2 Postmarketing Experience

The following adverse reactions have been identified during post-approval use of TWINRIX, HAVRIX, or ENGERIX-B. Because these reactions are reported voluntarily from a population of uncertain size, it is not possible to reliably estimate their frequency or establish a causal relationship to the vaccine.

Postmarketing Experience with TWINRIX

Infections and Infestations: Herpes zoster, meningitis.

Blood and Lymphatic System Disorders: Thrombocytopenia, thrombocytopenic purpura.

Immune System Disorders: Allergic reaction, anaphylactoid reaction, anaphylaxis, serum sickness–like syndrome days to weeks after vaccination (including arthralgia/arthritis, usually transient; fever; urticaria; erythema multiforme; ecchymoses; and erythema nodosum).

Nervous System Disorders: Bell's palsy, convulsions, encephalitis, encephalopathy, Guillain-Barré syndrome, hypoesthesia, myelitis, multiple sclerosis, neuritis, neuropathy, optic neuritis, paralysis, paresis, transverse myelitis.

Eye Disorders: Conjunctivitis, visual disturbances.

Ear and Labyrinth Disorders: Earache, tinnitus.

Cardiac Disorders: Palpitations, tachycardia.

Vascular Disorders: Vasculitis.

Respiratory, Thoracic, and Mediastinal Disorders: Bronchospasm, including asthma-like symptoms; dyspnea.

Gastrointestinal Disorders: Dyspepsia.

Hepatobiliary Disorders: Hepatitis, jaundice.

Skin and Subcutaneous Tissue Disorders: Alopecia, angioedema, eczema, erythema multiforme, erythema nodosum, hyperhidrosis, lichen planus.

Musculoskeletal and Connective Tissue Disorders: Arthritis, muscular weakness.

General Disorders and Administration Site Conditions: Chills; immediate injection site pain, stinging, and burning sensation; injection site reaction; malaise.

Investigations: Abnormal liver function tests.

Postmarketing Experience with HAVRIX and/or ENGERIX-B

The following list includes adverse reactions for HAVRIX and/or ENGERIX-B not already reported above for TWINRIX.

Eye Disorders: Keratitis.a

Skin and Subcutaneous Tissue Disorders: Stevens-Johnson syndrome.a

Congenital, Familial, and Genetic Disorders: Congenital abnormality.b

a Following ENGERIX-B.

b Following HAVRIX.

7 DRUG INTERACTIONS

7.1 Concomitant Administration with Vaccines and Immune Globulin

Do not mix TWINRIX with any other vaccine or product in the same syringe.

When concomitant administration of immunoglobulin is required, it should be given with a different syringe and at a different injection site.

There are no data to assess the concomitant use of TWINRIX with other vaccines.

7.2 Immunosuppressive Therapies

Immunosuppressive therapies, including irradiation, antimetabolites, alkylating agents, cytotoxic drugs, and corticosteroids (used in greater-than-physiologic doses), may reduce the immune response to TWINRIX.

7.3 Interference with Laboratory Tests

Hepatitis B surface antigen (HBsAg) derived from hepatitis B vaccines has been transiently detected in blood samples following vaccination. Serum HBsAg detection may not have diagnostic value within 28 days after receipt of a hepatitis B vaccine, including TWINRIX.

8 USE IN SPECIFIC POPULATIONS

8.1 Pregnancy

Risk Summary

All pregnancies have a risk of birth defect, loss, or other adverse outcomes. In the U.S. general population, the estimated background risk of major birth defects and miscarriage in clinically recognized pregnancies is 2% to 4% and 15% to 20%, respectively.

There are no adequate and well-controlled studies of TWINRIX in pregnant women in the U.S. Available data do not suggest an increased risk of major birth defects and miscarriage in women who received TWINRIX within 28 days prior to conception or during pregnancy (see Data).

A developmental toxicity study was performed in female rats administered TWINRIX prior to mating and during gestation (0.2 mL at each occasion). This study revealed no adverse effects on fetal or pre-weaning development (see Data).

Data

Human Data: A pregnancy exposure registry was maintained from 2001 to 2015. The registry prospectively enrolled 245 women who received a dose of TWINRIX during pregnancy or within 28 days prior to conception. After excluding induced abortions (n = 6, including one of a fetus with congenital anomalies), those lost to follow-up (n = 142), those with exposure in the third trimester (n = 1), and those with an unknown exposure timing (n = 9), there were 87 pregnancies with known outcomes with exposure within 28 days prior to conception, or in the first or second trimesters. Miscarriage was reported for 9.6% of pregnancies with exposure to TWINRIX prior to 20 weeks gestation (8/83). Major birth defects were reported for 3.8% of live born infants whose mothers were exposed within 28 days prior to conception or during the first or second trimester (3/80). The rates of miscarriage and major birth defects were consistent with estimated background rates.

In pre- and post-licensure clinical studies of TWINRIX, 45 pregnant women were inadvertently administered TWINRIX following their last menstrual period. Among such pregnancies, after excluding elective terminations (n = 1) and those lost to follow-up (n = 1), there were 43 pregnancies with known outcomes all with exposure in the first trimester. Miscarriage was reported in 16% of pregnancies (7/43) and major birth defects were reported in 2.6% of live births (1/38). The rates of miscarriage and major birth defects were consistent with estimated background rates.

Animal Data: In a developmental toxicity study, female rats were administered TWINRIX by intramuscular injection on Day 30 prior to mating and on gestation Days 6, 8, 11, and 15. The total dose was 0.2 mL (divided) at each occasion (a single human dose is 1 mL). No adverse effects on pre-weaning development up to post-natal Day 25 were observed. There were no fetal malformations or variations.

8.2 Lactation

Risk Summary

There is no information regarding the presence of TWINRIX in human milk, the effects on the breastfed child, or the effects on milk production. The developmental and health benefits of breastfeeding should be considered along with the mother’s clinical need for TWINRIX and any potential adverse effects on the breastfed child from TWINRIX or from the underlying maternal condition. For preventive vaccines, the underlying maternal condition is susceptibility to disease prevented by the vaccine.

8.4 Pediatric Use

Safety and effectiveness in pediatric patients younger than 18 years have not been established.

8.5 Geriatric Use

Clinical studies of TWINRIX did not include sufficient numbers of subjects aged 65 years and older to determine whether they respond differently from younger subjects [see Clinical Studies (14.1, 14.3)].

11 DESCRIPTION

TWINRIX [Hepatitis A & Hepatitis B (Recombinant) Vaccine] is a bivalent vaccine containing the antigenic components used in producing HAVRIX (Hepatitis A Vaccine) and ENGERIX-B [Hepatitis B Vaccine (Recombinant)]. TWINRIX is a sterile suspension for intramuscular administration that contains inactivated hepatitis A virus (strain HM175) and noninfectious HBsAg. The hepatitis A virus is propagated in MRC-5 human diploid cells and inactivated with formalin. The purified HBsAg is obtained by culturing genetically engineered Saccharomyces cerevisiae yeast cells, which carry the surface antigen gene of the hepatitis B virus. Bulk preparations of each antigen are adsorbed separately onto aluminum salts and then pooled during formulation.

A 1-mL dose of vaccine contains 720 ELISA Units of inactivated hepatitis A virus and 20 mcg of recombinant HBsAg protein. One dose of vaccine also contains 0.45 mg of aluminum in the form of aluminum phosphate and aluminum hydroxide as adjuvants, amino acids, sodium chloride, phosphate buffer, polysorbate 20, and Water for Injection. From the manufacturing process, each 1-mL dose of TWINRIX also contains residual formalin (not more than 0.1 mg), MRC-5 cellular proteins (not more than 2.5 mcg), neomycin sulfate (an aminoglycoside antibiotic included in the cell growth media; not more than 20 ng), and yeast protein (no more than 5%).

TWINRIX is available in prefilled syringes. The tip cap and rubber plunger stopper of the prefilled syringe are not made with natural rubber latex.

TWINRIX is formulated without preservatives.

12 CLINICAL PHARMACOLOGY

12.1 Mechanism of Action

Hepatitis A

The course of infection with hepatitis A virus (HAV) is extremely variable, ranging from asymptomatic infection to fulminant hepatitis.^3

The presence of antibodies to HAV (anti-HAV) confers protection against hepatitis A disease. However, the lowest titer needed to confer protection has not been determined. Natural infection provides lifelong immunity even when antibodies to hepatitis A are undetectable. Seroconversion is defined as antibody titers equal to or greater than the assay cut-off (cut-off values vary depending on the assay used) in those previously seronegative.

Hepatitis B

Infection with hepatitis B virus (HBV) can have serious consequences including acute massive hepatic necrosis and chronic active hepatitis. Chronically infected persons are at increased risk for cirrhosis and hepatocellular carcinoma.

Antibody concentrations ≥10 mIU/mL against HBsAg are recognized as conferring protection against hepatitis B virus infection.^4

13 NONCLINICAL TOXICOLOGY

13.1 Carcinogenesis, Mutagenesis, Impairment of Fertility

TWINRIX has not been evaluated for its carcinogenic or mutagenic potential, or for impairment of male fertility in animals. Vaccination of female rats with TWINRIX had no effect on fertility. [See Use in Specific Populations (8.1).]

14 CLINICAL STUDIES

14.1 Immunogenicity: Standard 0-, 1-, and 6-Month Dosing Schedule

In 11 clinical trials, sera from 1,551 healthy adults aged 17 to 70 years, including 555 male subjects and 996 female subjects, were analyzed following administration of 3 doses of TWINRIX on a 0-, 1-, and 6-month schedule. Seroconversion (defined as equal to or greater than assay cut-off depending on assay used) for antibodies against HAV was elicited in 99.9% of vaccinees, and protective antibodies (defined as ≥10 mIU/mL) against HBV surface antigen were detected in 98.5% of vaccinees, 1 month after completion of the 3-dose series (Table 2).

Table 2. Seroconversion and Seroprotection Rates in Worldwide Clinical Trials
Dose of TWINRIX | n | % Seroconversion; for Hepatitis Aa | % Seroprotection; for Hepatitis Bb
1 | 1,587 | 93.8 | 30.8
2 | 1,571 | 98.8 | 78.2
3 | 1,551 | 99.9 | 98.5
a Anti‑HAV titer ≥assay cut‑off: 20 mIU/mL (HAVAB Test) or 33 mIU/mL (ENZYMUN‑TEST).
b Anti‑HBsAg titer ≥10 mIU/mL (AUSAB Test).

One of the 11 trials was a comparative trial conducted in a U.S. population given either TWINRIX (on a 0-, 1-, and 6-month schedule) or HAVRIX (0- and 6-month schedule) and ENGERIX-B (0-, 1-, and 6-month schedule). The monovalent vaccines were given concurrently in opposite arms. Of the 773 adults (aged 18 to 70 years) enrolled in this trial, an immunogenicity analysis was performed in 533 subjects who completed the study according to protocol. Of these, 264 subjects received TWINRIX and 269 subjects received HAVRIX and ENGERIX-B. Seroconversion rates against HAV and seroprotection rates against HBV are presented in Table 3; geometric mean titers (GMTs) are presented in Table 4. The absolute difference in anti-HAV seropositivity rates between groups was 0.36% (90% CI: -1.8, 3.1). Non-inferiority in terms of anti-HAV response was demonstrated (lower limit of the 90% CI was higher than the pre-specified non-inferiority criterion of -4.3%). The absolute difference in anti-HBsAg seroprotection rates between groups was 2.8% (90% CI: -1.3, 7.7). Non-inferiority in terms of anti-HBV response was demonstrated (lower limit of the 90% CI was higher than the pre-specified non-inferiority criterion of -9.4%).

Table 3. Seroconversion and Seroprotection Rates in a U.S. Clinical Trial
Vaccine | n | Timepoint | % Seroconversion for Hepatitis Aa (95% CI) | % Seroprotection for Hepatitis Bb (95% CI)
TWINRIX | 264 | Month 1 | 91.6 | 17.9
TWINRIX |  | Month 2 | 97.7 | 61.2
TWINRIX |  | Month 7 | 99.6 (97.9, 100.0) | 95.1 (91.7, 97.4)
HAVRIX and ENGERIX-B | 269 | Month 1 | 98.1 | 7.5
HAVRIX and ENGERIX-B |  | Month 2 | 98.9 | 50.4
HAVRIX and ENGERIX-B |  | Month 7 | 99.3 (97.3, 99.9) | 92.2 (88.3, 95.1)
CI = Confidence Interval.
a Anti-HAV titer ≥assay cut-off: 33 mIU/mL (ENZYMUN-TEST).
b Anti-HBsAg titer ≥10 mIU/mL (AUSAB Test).

Table 4. Geometric Mean Titers in a U.S. Clinical Trial
Vaccine | n | Timepoint | GMT to Hepatitis A; (95% CI) | GMT to Hepatitis B; (95% CI)
TWINRIX | 263 | Month 1 | 335 | 8
TWINRIX | 259 | Month 2 | 636 | 23
TWINRIX | 264 | Month 7 | 4756 (4152, 5448) | 2099 (1663, 2649)
HAVRIX and ENGERIX-B | 268 | Month 1 | 444 | 6
HAVRIX and ENGERIX-B | 269 | Month 2 | 257 | 18
HAVRIX and ENGERIX-B | 269 | Month 7 | 2948 (2638, 3294) | 1871 (1428, 2450)
GMT = Geometric mean titer; CI = Confidence Interval.

Since the immune responses to hepatitis A and hepatitis B induced by TWINRIX were non-inferior to the monovalent vaccines, efficacy is expected to be similar to the efficacy for each of the monovalent vaccines.

The antibody titers achieved 1 month after the final dose of TWINRIX were higher than titers achieved 1 month after the final dose of HAVRIX in this clinical trial. This may have been due to a difference in the recommended dosage regimens for these 2 vaccines, whereby vaccinees receiving TWINRIX received 3 doses of 720 EL.U. of hepatitis A antigen at 0, 1, and 6 months, whereas vaccinees receiving HAVRIX received 2 doses of 1440 EL.U. of the same antigen (at 0 and 6 months). However, these differences in peak titer have not been shown to be clinically significant.

14.2 Immunogenicity: Accelerated Dosing Schedule (Day 0, 7, and 21 to 30, Month 12)

In 496 healthy adults, the safety and immunogenicity of TWINRIX given on a 0-, 7-, and 21- to 30-day schedule followed by a booster dose at 12 months (n = 250), was compared with separate vaccinations with monovalent hepatitis A vaccine (HAVRIX at 0 and 12 months) and hepatitis B vaccine (ENGERIX-B at 0, 1, 2, and 12 months) as a control group (n = 246).

Following a booster dose at Month 12, seroprotection rates for hepatitis B and seroconversion rates for hepatitis A at Month 13 following TWINRIX were non-inferior to the control group. The absolute difference in anti-HBs seroprotection rates between groups (HAVRIX + ENGERIX-B minus TWINRIX) was -2.99 (95% CI: -7.80, 1.49). Non-inferiority was demonstrated as the upper limit of the 95% CI was lower than the pre-defined limit of 7%. The absolute difference in anti-HAV seroprotection rates between groups (HAVRIX + ENGERIX-B minus TWINRIX) was 0 (95% CI: -1.91, 1.94). Non-inferiority was demonstrated as the upper limit of the 95% CI was lower than the pre-defined limit of 7%. The immune responses are presented in Table 5.

Table 5. Seroconversion and Seroprotection Rates up to 1 Month after the Last Dose of Vaccines (According-to-Protocol Cohort)
 | Timepoint | TWINRIXa; (n = 194-204) | HAVRIX and ENGERIX-Bb; (n = 197-207)
% Seroconversion for Hepatitis Ac (95% CI) | Day 37 | 98.5 (95.8, 99.7) | 98.6 (95.8, 99.7)
% Seroconversion for Hepatitis Ac (95% CI) | Day 90 | 100 (98.2, 100) | 95.6 (91.9, 98.0)
% Seroconversion for Hepatitis Ac (95% CI) | Month 12 | 96.9 (93.4, 98.9) | 86.9 (81.4, 91.2)
% Seroconversion for Hepatitis Ac (95% CI) | Month 13 | 100 (98.1, 100) | 100 (98.1, 100)
% Seroprotection for Hepatitis Bd (95% CI) | Day 37 | 63.2 (56.2, 69.9) | 43.5 (36.6, 50.5)
% Seroprotection for Hepatitis Bd (95% CI) | Day 90 | 83.2 (77.3, 88.1) | 76.7 (70.3, 82.3)
% Seroprotection for Hepatitis Bd (95% CI) | Month 12 | 82.1 (75.9, 87.2) | 77.8 (71.3, 83.4)
% Seroprotection for Hepatitis Bd (95% CI) | Month 13 | 96.4 (92.7, 98.5) | 93.4 (89.0, 96.4)
CI = Confidence Interval.
a TWINRIX given on a 0-, 7-, and 21- to 30-day schedule followed by a booster at Month 12.
b HAVRIX 1440 EL.U./1 mL given on a 0- and 12-month schedule and ENGERIX-B 20 mcg/1 mL given on a 0-, 1-, 2-, and 12-month schedule.
c Anti-HAV titer ≥assay cut-off: 15 mIU/mL (anti-HAV Behring Test).
d Anti‑HBsAg titer ≥10 mIU/mL (AUSAB Test).

14.3 Immunogenicity in Adults Older than 40 Years

The effect of age on immune response to TWINRIX was studied in 2 trials. The first trial evaluated subjects aged 41 to 63 years (N = 72; mean age = 50). All subjects were seropositive for anti-HAV antibodies following the third dose of TWINRIX. For the hepatitis B response, 94% of subjects were seroprotected after the third dose of TWINRIX.

The second trial included subjects aged 19 years and older with a comparison between those older than 40 years (n = 183, aged 41 to 70 years; mean age: 48) and those aged 40 years or younger (n = 191; aged 19 to 40 years; mean age: 33). More than 99% of subjects in both age groups achieved a seropositive response for anti-HAV antibodies, and GMTs were comparable between the age groups. In the older subjects who received TWINRIX, 92.9% (95% CI: 88.2, 96.2) achieved seroprotection against hepatitis B compared with 96.9% (95% CI: 93.3, 98.8) of the younger subjects. The GMT was 1,890 mIU/mL in the older subjects compared with 2,285 mIU/mL in the younger subjects.

14.4 Duration of Immunity

Two clinical trials involving a total of 129 subjects demonstrated that antibodies to both HAV and HBV surface antigen persisted for at least 4 years after the first vaccine dose in a 3-dose series of TWINRIX, given on a 0-, 1-, and 6-month schedule. For comparison, after the recommended immunization regimens for HAVRIX and ENGERIX-B, respectively, similar studies involving a total of 114 subjects have shown that seropositivity to HAV and HBV also persists for at least 4 years.

15 REFERENCES

1. Ascherio A, Zhang SM, Hernán MA, et al. Hepatitis B vaccination and the risk of multiple sclerosis. N Engl J Med. 2001;344(5):327-332.
2. Confavreux C, Suissa S, Saddier P, et al. Vaccination and the risk of relapse in multiple sclerosis. N Engl J Med. 2001;344(5):319-326.
3. Lemon SM. Type A viral hepatitis: new developments in an old disease. N Engl J Med. 1985;313(17):1059-1067.
4. Frisch-Niggemeyer W, Ambrosch F, Hofmann H. The assessment of immunity against hepatitis B after vaccination. J Bio Stand. 1986;14(3):255-258.

16 HOW SUPPLIED/STORAGE AND HANDLING

TWINRIX is available in 1-mL single-dose prefilled disposable TIP‑LOK syringes (Luer Lock syringes) packaged without needles (Preservative-Free Formulation). TIP-LOK syringes are to be used with Luer Lock compatible needles.

The tip cap and rubber plunger stopper of the prefilled syringe are not made with natural rubber latex.

NDC 58160-815-43 Syringe in Package of 10: NDC 58160-815-52

Store refrigerated between 2° and 8°C (36° and 46°F). Do not freeze; discard if product has been frozen.

17 PATIENT COUNSELING INFORMATION

- Inform vaccine recipients of the potential benefits and risks of immunization with TWINRIX.
- Emphasize, when educating vaccine recipients regarding potential side effects, that components of TWINRIX cannot cause hepatitis A or hepatitis B infection.
- Instruct vaccine recipients to report any adverse events to their healthcare provider.
- Give vaccine recipients the Vaccine Information Statements, which are required by the National Childhood Vaccine Injury Act of 1986 to be given prior to immunization. These materials are available free of charge at the Centers for Disease Control and Prevention (CDC) website (www.cdc.gov/vaccines).

TWINRIX, HAVRIX, ENGERIX-B, and TIP-LOK are trademarks owned by or licensed to the GSK group of companies. The other brands listed are trademarks owned by or licensed to their respective owners and are not owned by or licensed to the GSK group of companies. The makers of these brands are not affiliated with and do not endorse the GSK group of companies or its products.

Manufactured by GlaxoSmithKline Biologicals

Rixensart, Belgium, U.S. License No. 1617

Distributed by GlaxoSmithKline

Durham, NC 27701

©2024 GSK group of companies or its licensor.

TWR:29PI

PACKAGE LABEL

PRINCIPAL DISPLAY PANEL

NDC 58160-815-52

Hepatitis A & Hepatitis B (Recombinant) Vaccine

TWINRIX

HepA/HepB

Rx only

For 18 Years of Age and Older

10 Disposable Single-Dose Prefilled TIP-LOK Syringes each containing one 1-mL dose

TIP-LOK Syringes to be used with Luer Lock compatible needles

NEEDLES NOT INCLUDED

GSK

TWINRIX

Made in Germany

©2025 GSK group of companies or its licensor.

Rev. 8/25

525160